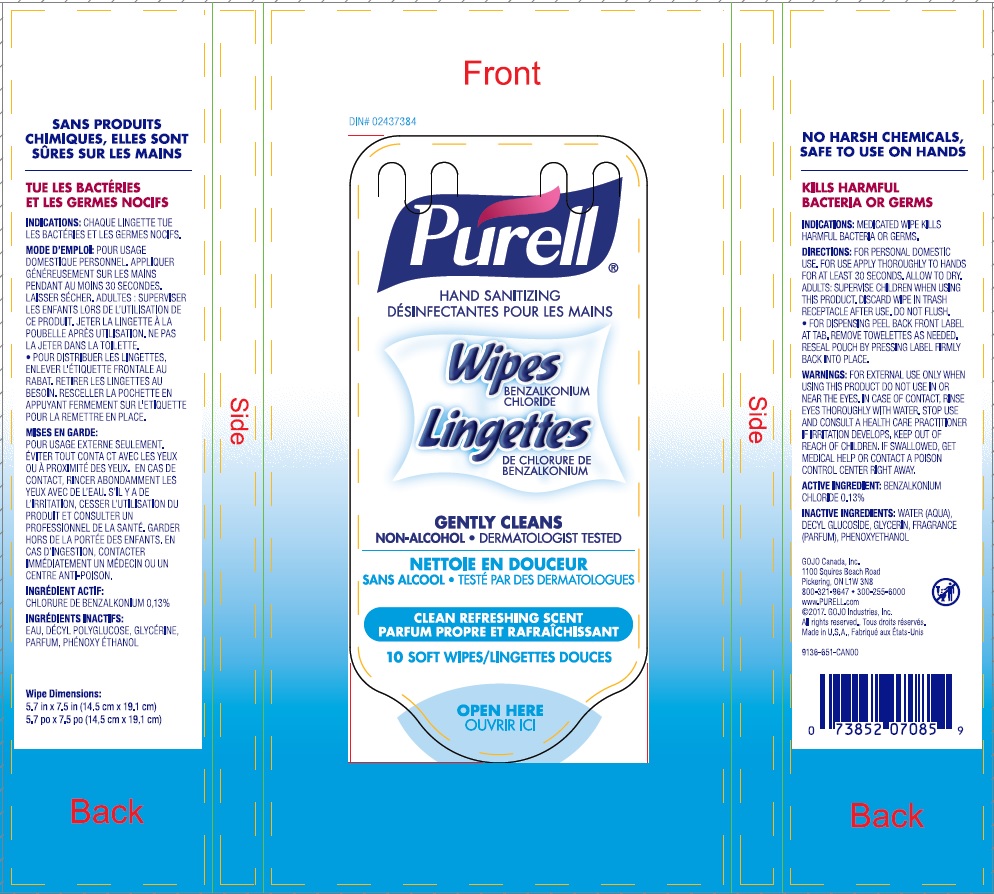 DRUG LABEL: PURELL Hand Sanitizing Wipes Clean Refreshing Scent
NDC: 21749-302 | Form: CLOTH
Manufacturer: GOJO Industries, Inc.
Category: otc | Type: HUMAN OTC DRUG LABEL
Date: 20241231

ACTIVE INGREDIENTS: BENZALKONIUM CHLORIDE 0.13 mg/100 mL
INACTIVE INGREDIENTS: WATER; DECYL GLUCOSIDE; GLYCERIN; PHENOXYETHANOL

PURELL Hand Sanitizing Wipes Clean Refreshing Scent